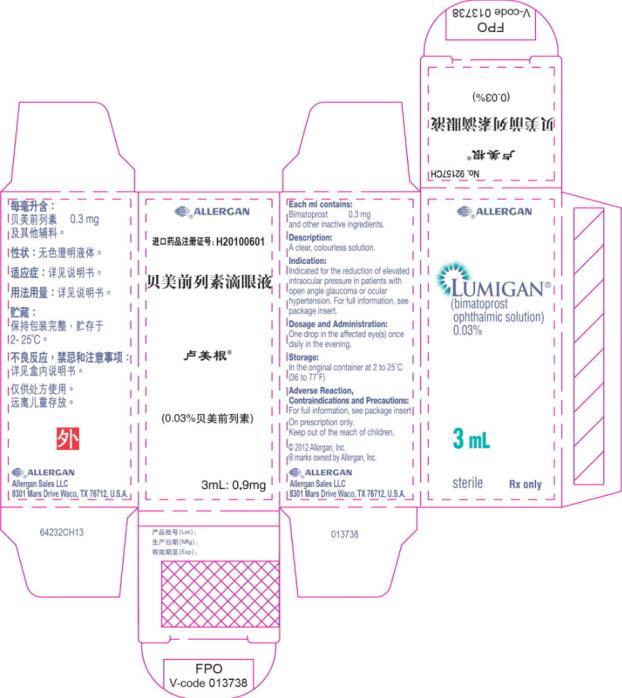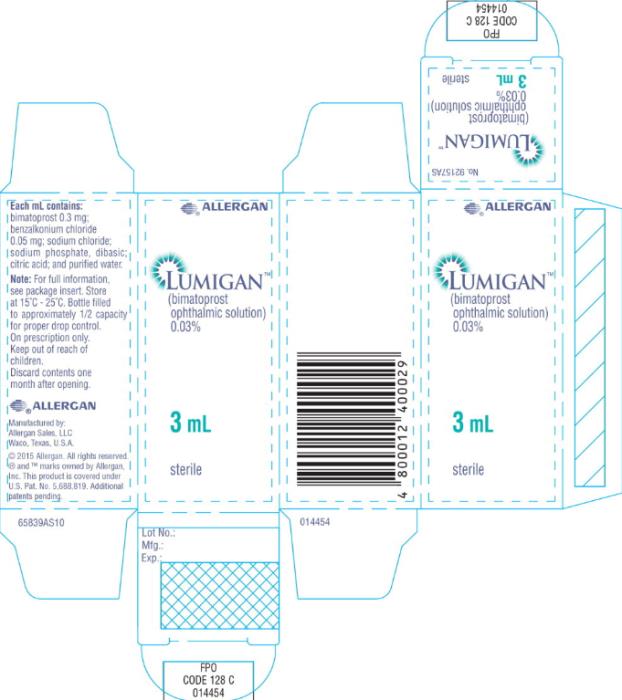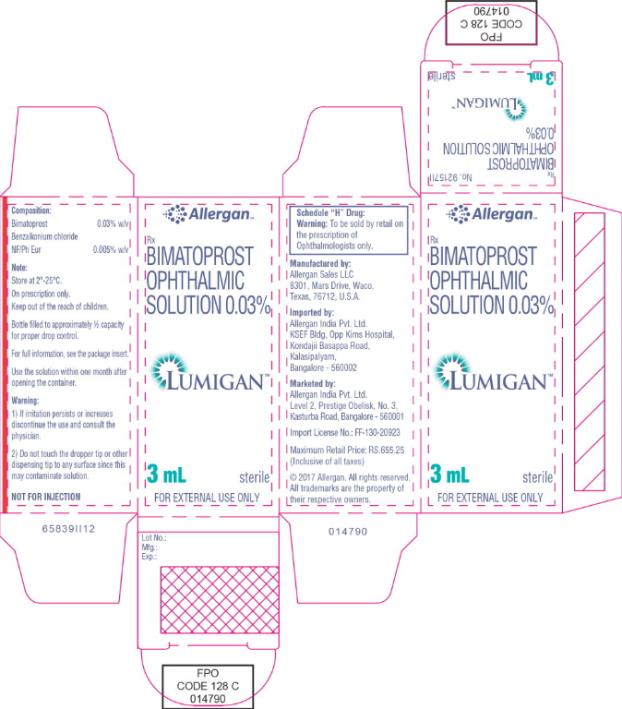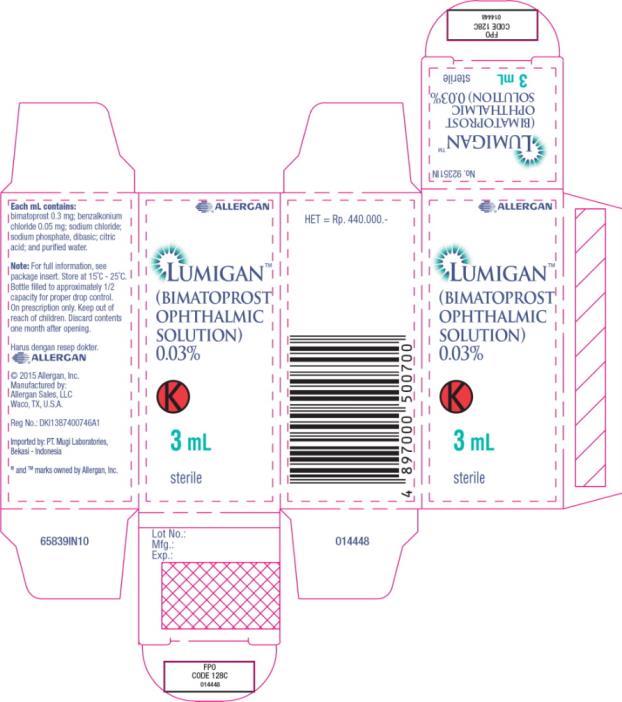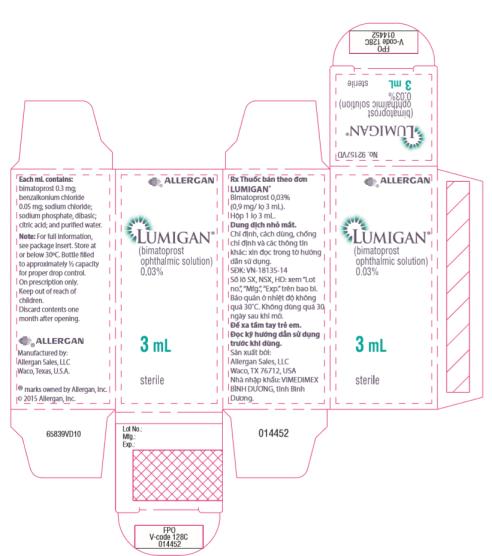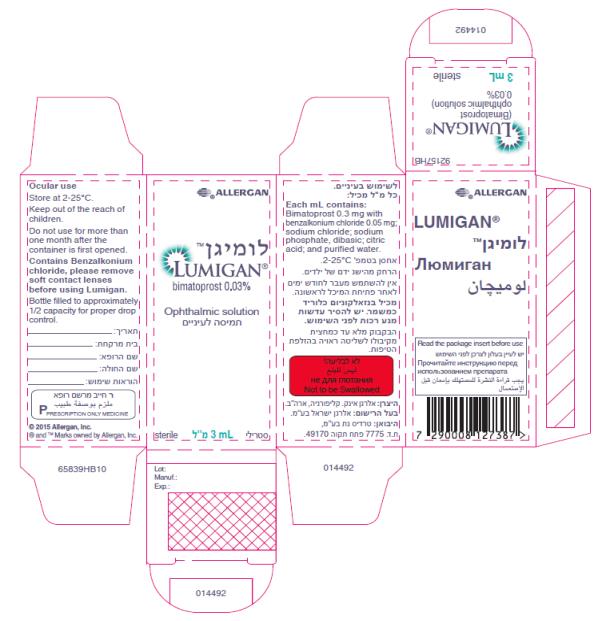 DRUG LABEL: LUMIGAN
NDC: 0023-9187 | Form: SOLUTION/ DROPS
Manufacturer: Allergan, Inc.
Category: prescription | Type: HUMAN PRESCRIPTION DRUG LABEL
Date: 20181207

ACTIVE INGREDIENTS: BIMATOPROST 0.3 mg/1 mL
INACTIVE INGREDIENTS: SODIUM CHLORIDE; BENZALKONIUM CHLORIDE; SODIUM PHOSPHATE, DIBASIC; CITRIC ACID MONOHYDRATE; WATER; SODIUM HYDROXIDE; HYDROCHLORIC ACID

Lumigan 03

Principal Display Panel - 0.3 mg/1 mL Carton Label

®ALLERGAN

LUMIGAN®
(bimatoprost
ophthalmic solution)

0.03%

3 mL

sterile Rx only

Principal Display Panel - 0.3 mg/1 mL Carton Label

ALLERGAN™

Rx

bimatoprost
ophthalmic solution

0.03%

LUMIGAN™

3 mL

sterile

Principal Display Panel - 0.3 mg/1 mL Carton Label

® ALLERGAN

LUMIGAN™

Rx

(BIMATOPROST
OPHTHALMIC
SOLUTION)
0.03%

3 mL

sterile

Principal Display Panel - 0.3 mg/1 mL Carton Label

® ALLERGAN

LUMIGAN™

(BIMATOPROST
OPHTHALMIC
SOLUTION)
0.03%

K

3 mL

sterile

Principal Display Panel - 0.3 mg/1 mL Carton Label

® ALLERGAN

LUMIGAN™

(bimatoprost
ophthalmic solution
SOLUTION)
0.03%

3 mL

sterile

Principal Display Panel - 0.3 mg/1 mL Carton Label

® ALLERGAN

LUMIGAN™

(bimatoprost 0.03%
Ophthalmic solution

3 mL

sterile